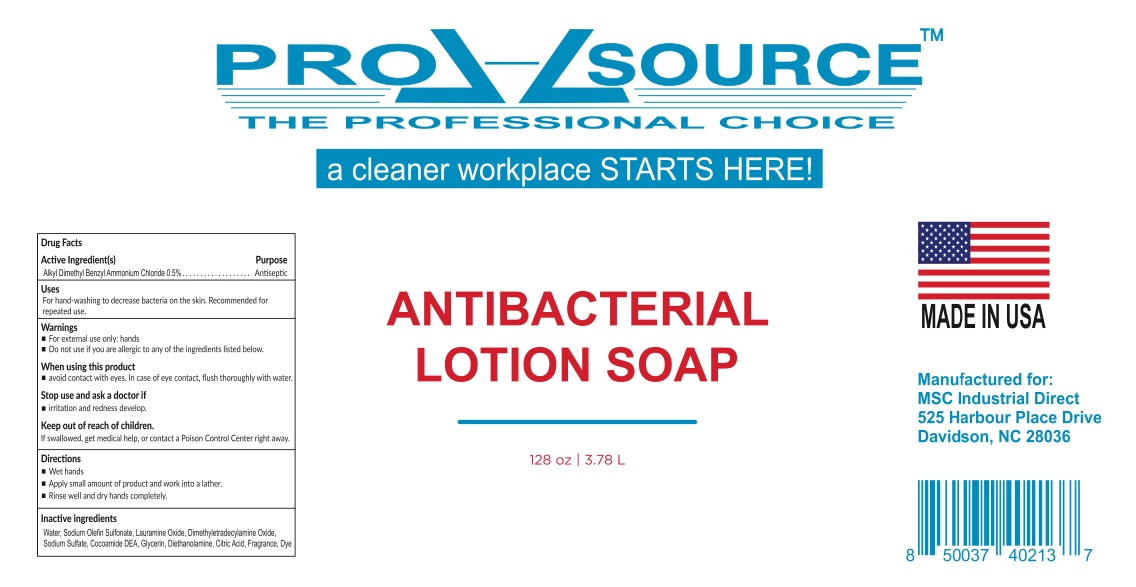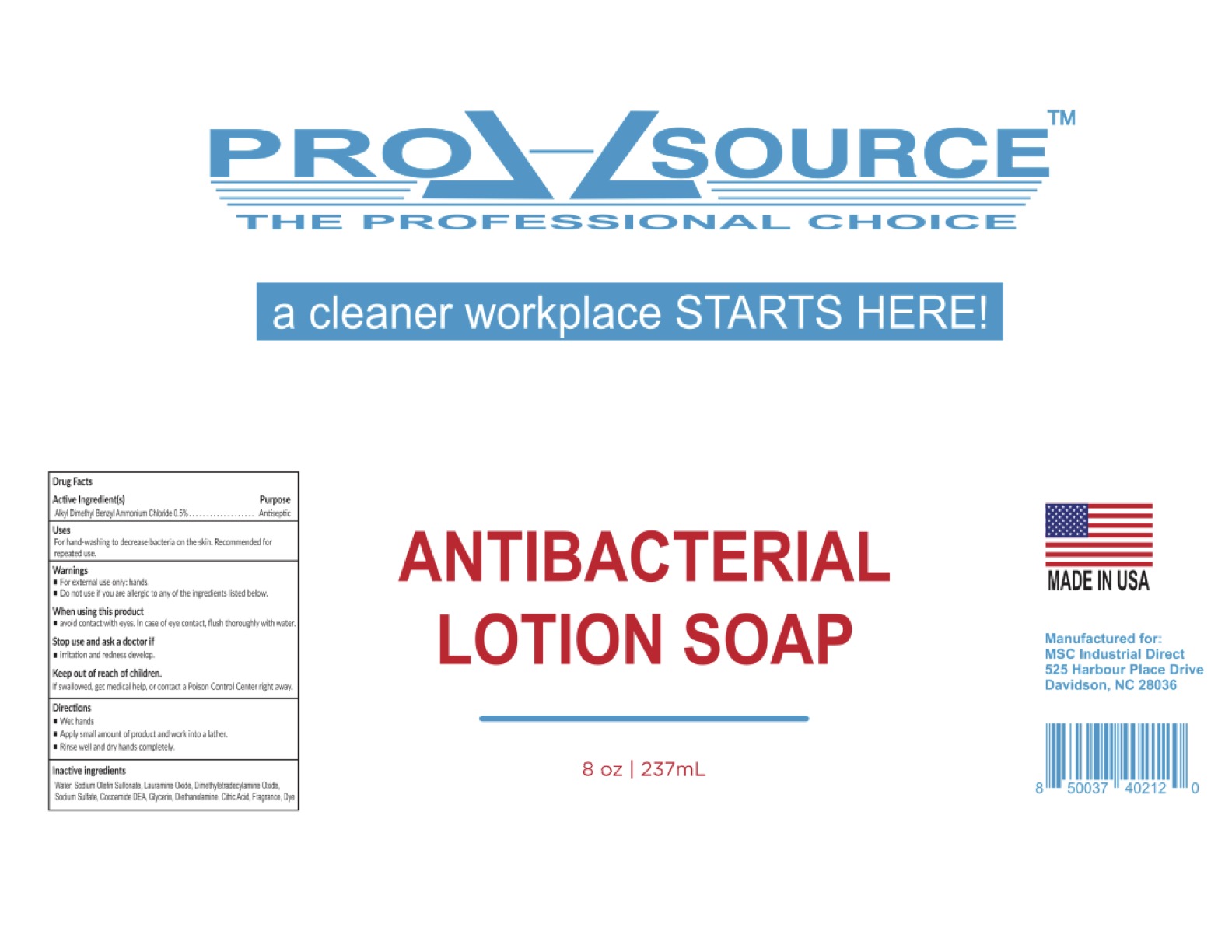 DRUG LABEL: gel
NDC: 75594-190 | Form: GEL
Manufacturer: Commercial Beverage Concepts LLC
Category: otc | Type: HUMAN OTC DRUG LABEL
Date: 20220822

ACTIVE INGREDIENTS: BENZALKONIUM CHLORIDE 5 kg/1000 kg
INACTIVE INGREDIENTS: LAURAMINE OXIDE; SODIUM DODECYLBENZENESULFONATE; ANHYDROUS CITRIC ACID; GLYCERIN; SODIUM SULFATE

ACTIVE INGREDIENT

Alkyl Dimethyl Benzyl Ammonium Chloride 0.5%

PURPOSE

For hand-washing to decrease bacteria on the skin. Rocommended for repeated use.

WARNINGS

- For external use only: hands
- Do not use if you are allergic to any of the ingedients listed below

When using this product:

- avoid contact with eyes. In case of eye contact, flush thoroughly with water

Stop use and ask a doctor if:

- irritation and redness develop

Directions:

- Wet hands
- Rinse well and dry hands completely

INACTIVE INGREDIENT

Water, Sodium Olefin Sulfonate, Lauramine Oxide, Dimethyletradecylamine Oxide, Sodium Sulfonate, Cocamide DEA, Glycerin, Diethanolamine, Citric Acid, Fragrance, Dye

Keep out of reach of children:

If swallowed, get medical help, or contact a Poison Control Center right away

DOSAGE AND ADMINISTRATION

Apply small amount of product and work into a lather